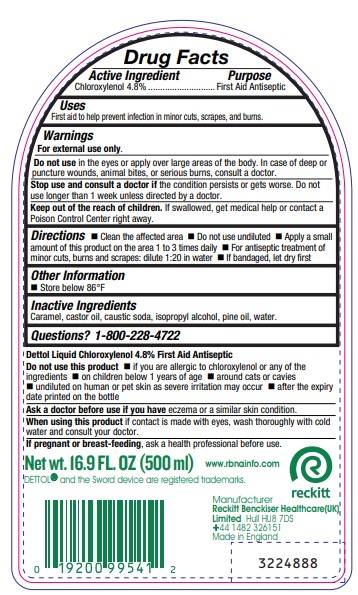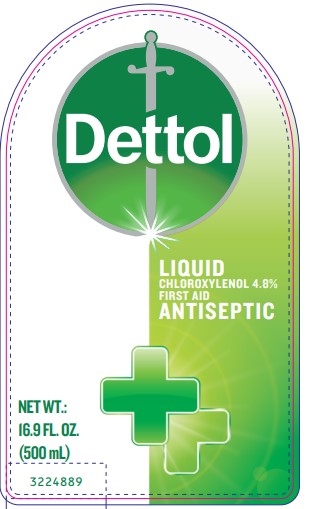 DRUG LABEL: Dettol First Aid Antiseptic
NDC: 52031-0876 | Form: LIQUID
Manufacturer: Reckitt Benckiser (UK) Ltd.
Category: otc | Type: HUMAN OTC DRUG LABEL
Date: 20240124

ACTIVE INGREDIENTS: CHLOROXYLENOL 4.8 g/15 mL
INACTIVE INGREDIENTS: CARAMEL; CASTOR OIL; SODIUM HYDROXIDE; ISOPROPYL ALCOHOL; WHITE PINE OIL; WATER

Drug Facts

Active Ingredient

Chloroxylenol 4.8%

Purpose

First Aid Antiseptic

Uses

First aid to help prevent infection in minor cuts, scrapes, and burns.

Warnings

For external use only.

DO NOT USE

Do not usein the eyes or apply over large areas of the body. In case of deep or puncture wounds, animal bites, or serious burns, consult a doctor.

WHEN USING

First Aid to help prevent infection of minocutsscrapesburns

Stop use and consult a doctor ifthe condition persists or gets worse. Do not use longer than 1 week unless directed by a doctor.

KEEP OUT OF REACH OF CHILDREN

Keep out of the reach of children.If swallowed, get medical help or contact a Poison Control Center right away.

Directions

- Clean the affected area
- Do not use undiluted
- Apply a small amount of this product on the area 1 to 3 times daily
- For antiseptic treatment of minor cuts, burns and scrapes: dilute 1:20 in water
- If bandaged, let dry first

Other information

- Store below 86°F

Inactive Ingredients

Caramel, castor oil, caustic soda, isopropyl alcohol, pine oil, water.

Questions? 1-800-228-4722

Do not use this product

- if you are allergic to chloroxylenol or any of the ingredients
- on children below 1 years of age
- around cats or cavies
- undiluted on human or pet skin as severe irritation may occur
- after the expiry date printed on the bottle

Ask a doctor before use if you haveeczema or a similar skin condition.

WHEN USING

When using this productif contact is made with eyes, wash thoroughly with cold water and consult your doctor.

PREGNANCY OR BREAST FEEDING

If pregnant or breast-feeding,ask a health professional before use.

Package Label - Principal Display Panel

Dettol
LIQUID
CHLOROXYLENOL 4.8%
FIRST AID
ANTISEPTIC
NET WT.:
16.9 FL. OZ.
(500 mL)
3224889

Dettol Liquid Chloroxylenol 4.8% First Aid Antiseptic
Net wt.16.9 FL. OZ (500ml)
www.rbnainfo.com
DETTOL®and the Sword device are registered trademarks.
reckitt
Manufacturer
Reckitt Benckiser Healthcare(UK)
Limited Hull HU8 7DS
+44 1482 326151
Made in England
3224888